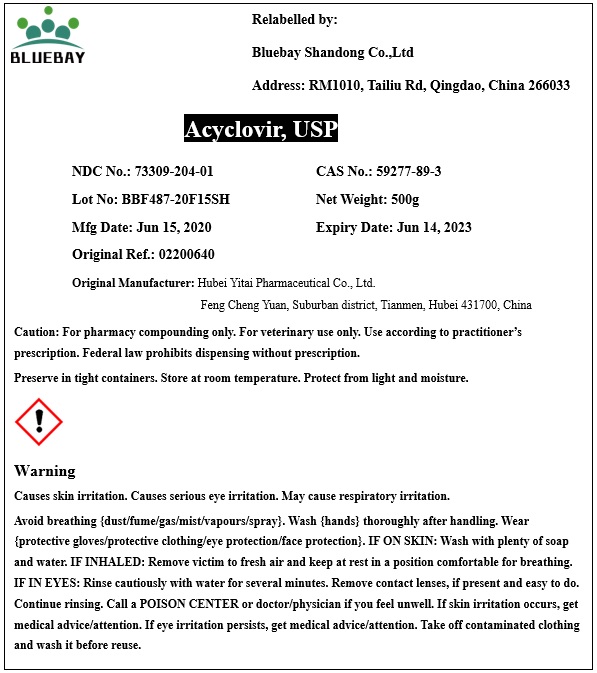 DRUG LABEL: Acyclovir
NDC: 73309-204 | Form: POWDER
Manufacturer: BLUEBAY SHANDONG CO.,LTD
Category: other | Type: BULK INGREDIENT
Date: 20201021

ACTIVE INGREDIENTS: ACYCLOVIR 1 g/1 g

Acyclovir